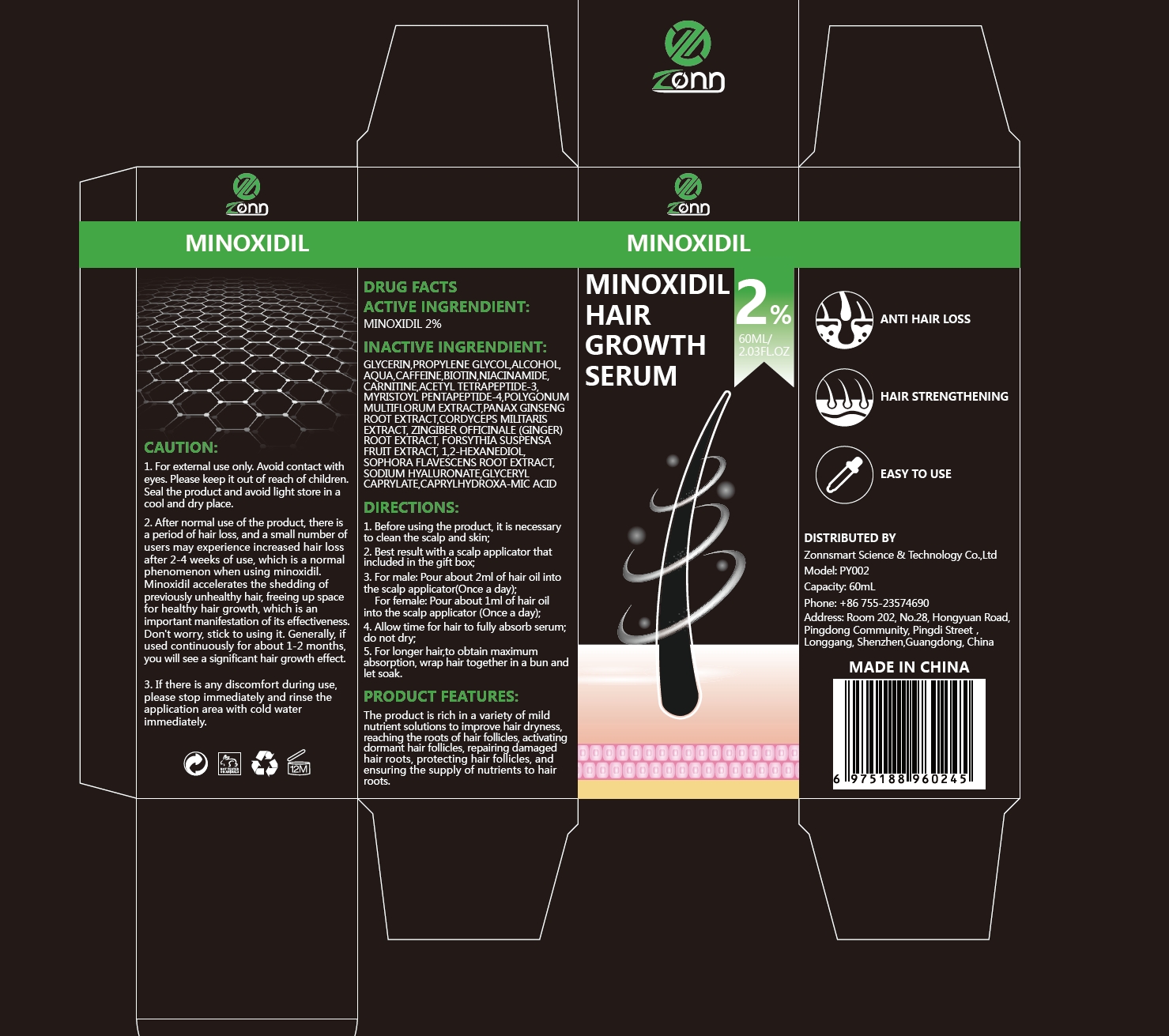 DRUG LABEL: 2% Minoxidil hair growth serum
NDC: 84693-003 | Form: LIQUID
Manufacturer: Zonnsmart Science & Technology Co.,Ltd
Category: otc | Type: HUMAN OTC DRUG LABEL
Date: 20240830

ACTIVE INGREDIENTS: MINOXIDIL 2 g/100 mL
INACTIVE INGREDIENTS: WATER; MYRISTOYL PENTAPEPTIDE-4; FORSYTHIA SUSPENSA FRUIT; 1,2-HEXANEDIOL; CAPRYLHYDROXAMIC ACID; PROPYLENE GLYCOL; ACETYL TETRAPEPTIDE-3; ASIAN GINSENG; SOPHORA FLAVESCENS ROOT; GLYCERYL CAPRYLATE; GLYCERIN; CORDYCEPS MILITARIS FRUITING BODY; NIACINAMIDE; CARNITINE; GINGER; CAFFEINE; ALCOHOL; HYALURONATE SODIUM; REYNOUTRIA MULTIFLORA WHOLE; BIOTIN

2% Minoxidil hair growth serum

ACTIVE INGREDIENT

Minoxidil 2%

PURPOSE

ANTI HAIR LOSS, HAIR STRENGTHENING

Please keep it out of reach of children

INDICATIONS AND USAGE

ANTI HAIR LOSS, HAIR STRENGTHENING, EASY TO USE

WARNINGS

1. For extemal use only. Avoid contact witheyes. Please keep it out of reach of children.Seal the product and avoid light store in acool and dry place.

DOSAGE AND ADMINISTRATION

1. Before using the product, it is necessaryto clean the scalp and skin;
2. Best result with a scalp applicator thatincluded in the gift box;
3. For male: Pour about 2ml of hair oil intothe scalp applicator(Once a day);For female: Pour about 1ml of hair oilinto the scalp applicator (Once a day);
4. Allow time for hair to fully absorb serum;do not dry;
5. For longer hair,to obtain maximumabsorption, wrap hair together in a bun andlet soak.

STORAGE AND HANDLING

Seal the product and avoid light store in acool and dry place.

INACTIVE INGREDIENT

GLYCERIN
PROPYLENE GLYCOL
ALCOHOL
AQUA
CAFFEINE
BIOTIN
NIACINAMIDE
CARNITINE
ACETYL TETRAPEPTIDE-3
MYRISTOYL PENTAPEPTIDE-4
POLYGONUM MULTIFLORUM EXTRACT
PANAX GINSENG ROOT EXTRACT
CORDYCEPS MILITARIS EXTRACT
ZINGIBER OFFICINALE (GINGER) ROOT EXTRACT
FORSYTHIA SUSPENSA FRUIT EXTRACT
1,2-HEXANEDIOL
SOPHORA FLAVESCENS ROOT EXTRACT
SODIUM HYALURONATE
GLYCERYL CAPRYLATE
CAPRYLHYDROXAMIC ACID